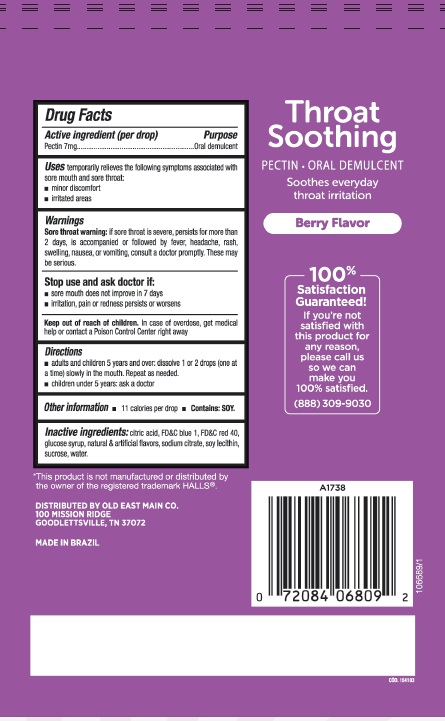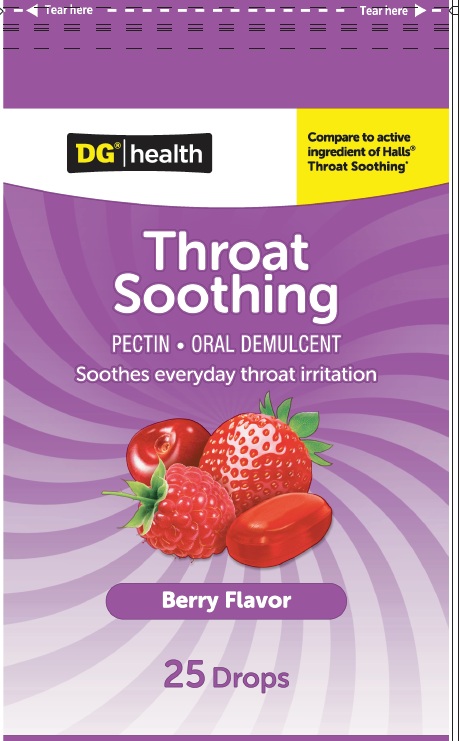 DRUG LABEL: Cough Drops Dollar General Berries Flavor 25ct
NDC: 75712-436 | Form: LOZENGE
Manufacturer: Dollar General Corporation
Category: otc | Type: HUMAN OTC DRUG LABEL
Date: 20250613

ACTIVE INGREDIENTS: PECTIN 7 mg/1 1
INACTIVE INGREDIENTS: SUCROSE; CORN SYRUP; CITRIC ACID; SOYBEAN LECITHIN; FD&C BLUE NO. 1; FD&C RED NO. 40; SODIUM CITRATE, UNSPECIFIED FORM

Drug Facts

Active Ingredient

Pectin 7mg

Purpose

Oral demulcent

Use

Temporarily relieves the following symptoms associated with sore mouth and sore throat:

- minor discomfort
- irritated areas

Warnings

Sore throat warning: if sore throat is severe, persists for more than 2 days, is accompanied or followed by fever, headache, rash, swelling, nausea or vomiting, consult a doctor promptly. These may be serious.

Stop use and ask doctor if: Sore mouth does not improve in 7 days Irritation, pain or redness persists or worsens

Keep out of reach of children. In case of overdose, get medical help or contact a Poison Control Center right away.

Directions

- Adults and children 5 years and over: dissolve 1 or 2 drops (one at a time) slowly in mouth. Repeat as needed.
- Children under 5 years: ask a doctor

Other information

- 11 calories per drop
- Contains : Soy

Inactive ingredients

Citric acid, FD&C blue 1, FD&C red 40, glucose syrup, natural & artificial flavors, sodium citrate, soy lecithin, sucrose, water.